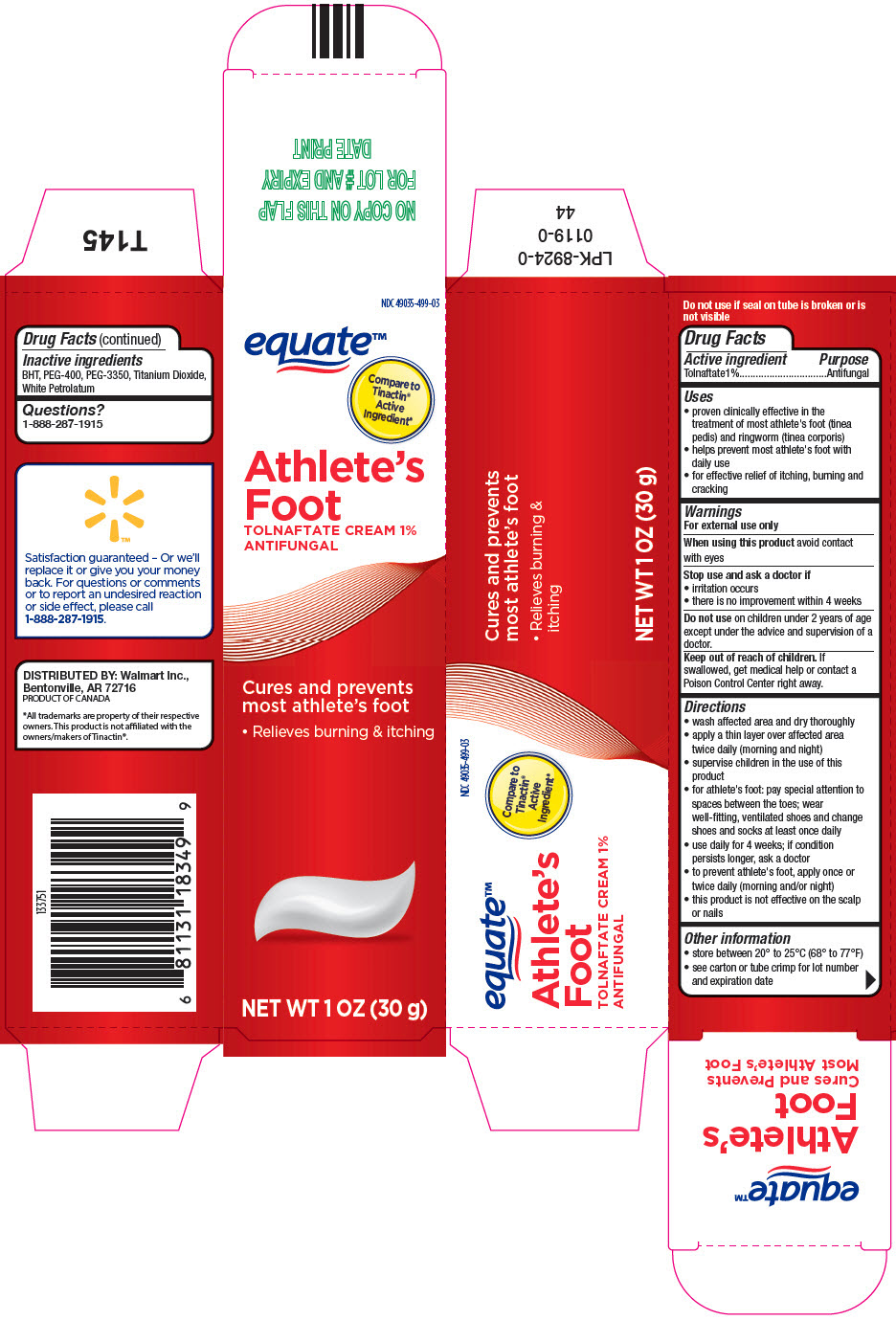 DRUG LABEL: equate

NDC: 49035-499 | Form: CREAM
Manufacturer: Wal-Mart Stores Inc
Category: otc | Type: HUMAN OTC DRUG LABEL
Date: 20250911

ACTIVE INGREDIENTS: TOLNAFTATE 10 mg/1 g
INACTIVE INGREDIENTS: BUTYLATED HYDROXYTOLUENE; POLYETHYLENE GLYCOL 400; TITANIUM DIOXIDE; PETROLATUM

equate™
Athlete's Foot

Drug Facts

Active ingredient

Tolnaftate1%

Purpose

Antifungal

Uses

- proven clinically effective in the treatment of most athlete's foot (tinea pedis) and ringworm (tinea corporis)
- helps prevent most athlete's foot with daily use
- for effective relief of itching, burning and cracking

Warnings

For external use only

When using this productavoid contact with eyes

Stop use and ask a doctor if

- irritation occurs
- there is no improvement within 4 weeks

DO NOT USE

Do not useon children under 2 years of age except under the advice and supervision of a doctor.

Keep out of reach of children.If swallowed, get medical help or contact a Poison Control Center right away.

Directions

- wash affected area and dry thoroughly
- apply a thin layer over affected area twice daily (morning and night)
- supervise children in the use of this product
- for athlete's foot: pay special attention to spaces between the toes; wear well-fitting, ventilated shoes and change shoes and socks at least once daily
- use daily for 4 weeks; if condition persists longer, ask a doctor
- to prevent athlete's foot, apply once or twice daily (morning and/or night)
- this product is not effective on the scalp or nails

Other information

- store between 20° to 25°C (68° to 77°F)
- see carton or tube crimp for lot number and expiration date

Inactive ingredients

BHT, PEG-400, PEG-3350, Titanium Dioxide, White Petrolatum

Questions?

1-888-287-1915

DISTRIBUTED BY: Walmart Inc.,
Bentonville, AR 72716

PRINCIPAL DISPLAY PANEL - 30 g Tube Carton

NDC 49035-499-03

equate™

Compare to
Tinactin®
Active
Ingredient*

Athlete's
Foot
TOLNAFTATE CREAM 1%
ANTIFUNGAL

Cures and prevents
most athlete's foot

- Relieves burning & itching

NET WT 1 OZ (30 g)